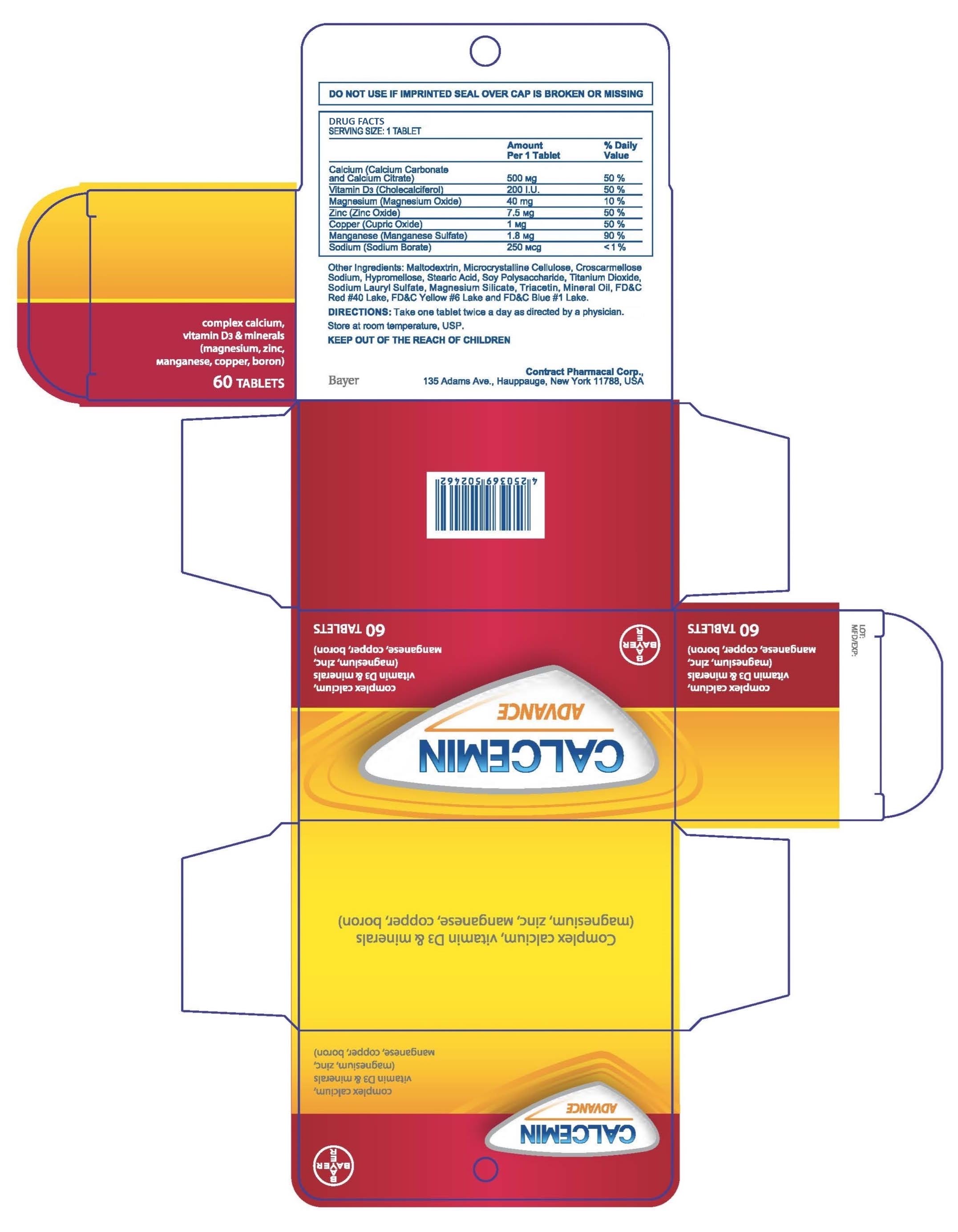 DRUG LABEL: Calcemin Advance
NDC: 0280-0272 | Form: TABLET, FILM COATED
Manufacturer: Bayer HealthCare LLC.
Category: otc | Type: HUMAN OTC DRUG LABEL
Date: 20250916

ACTIVE INGREDIENTS: CALCIUM CARBONATE 500 mg/1 1; PREVITAMIN D3 3 mg/1 1; MAGNESIUM OXIDE 40 mg/1 1; ZINC OXIDE 7.5 mg/1 1; SODIUM BORATE 2.45 mg/1 1
INACTIVE INGREDIENTS: CROSCARMELLOSE SODIUM; STEARIC ACID; SODIUM LAURYL SULFATE; HYPROMELLOSES; TITANIUM DIOXIDE; TRIACETIN; MAGNESIUM SILICATE; MINERAL OIL; FD&C RED NO. 40; FD&C YELLOW NO. 6; FD&C BLUE NO. 1; WATER; MALTODEXTRIN

Calcemin Advance

Drug Facts